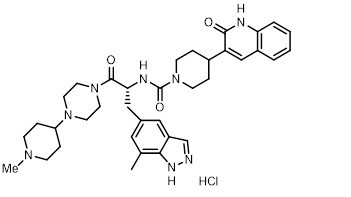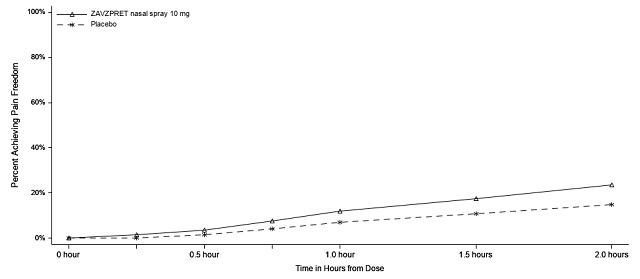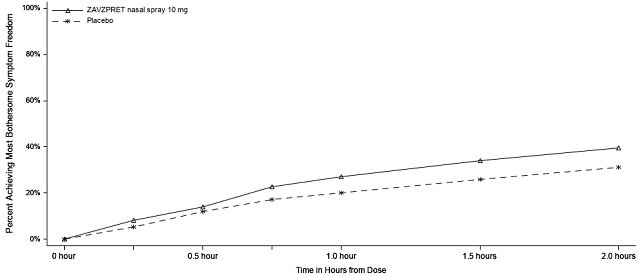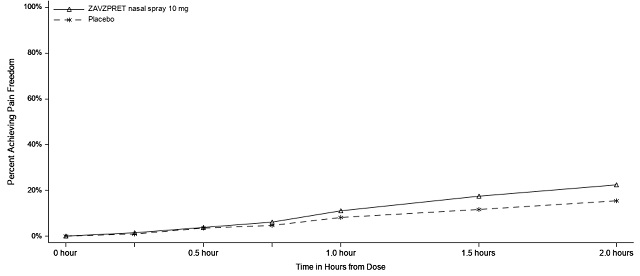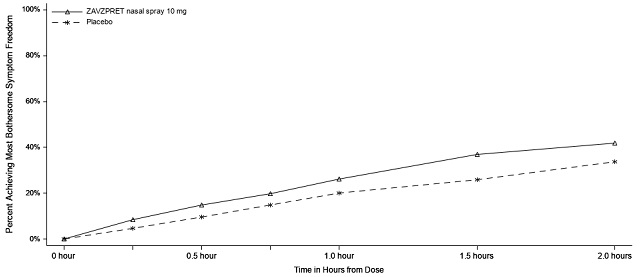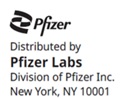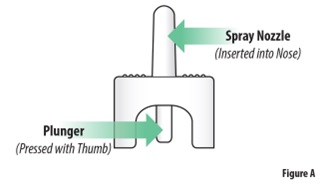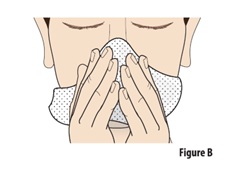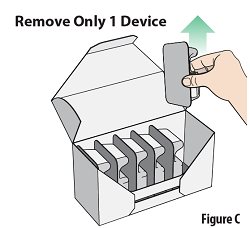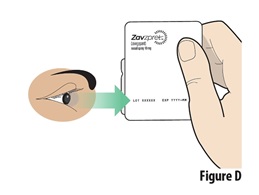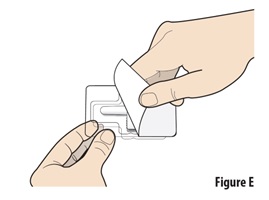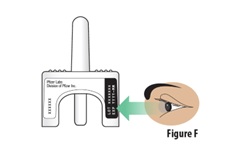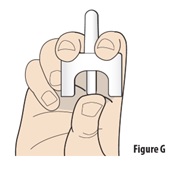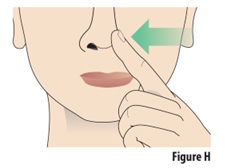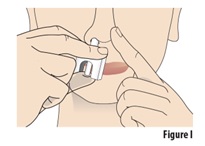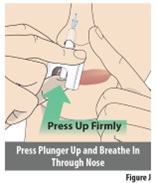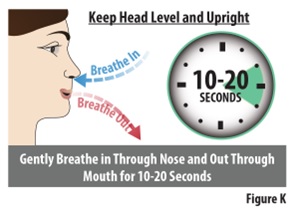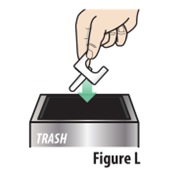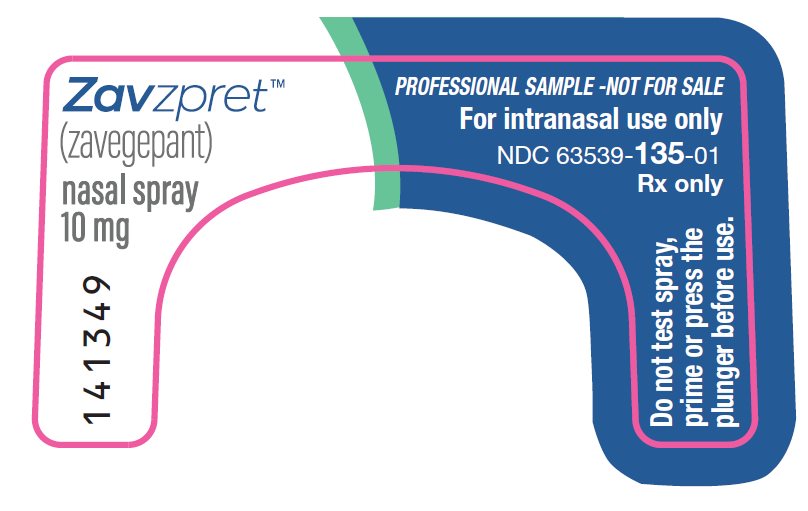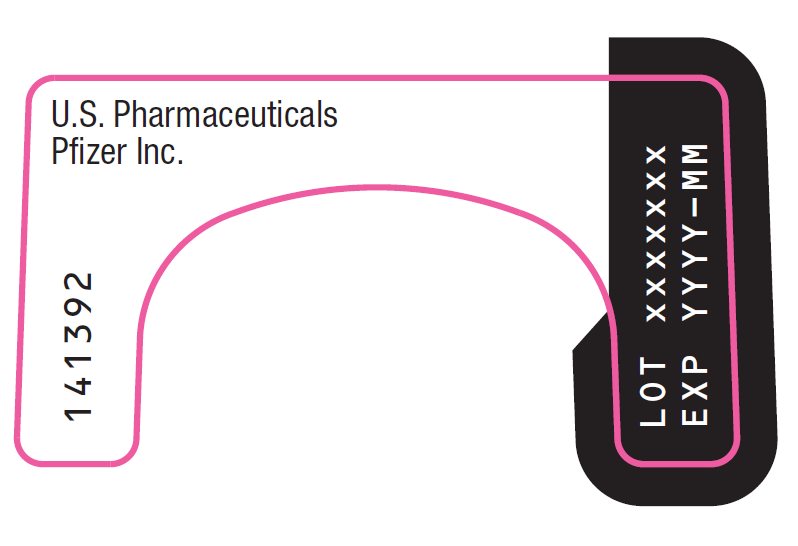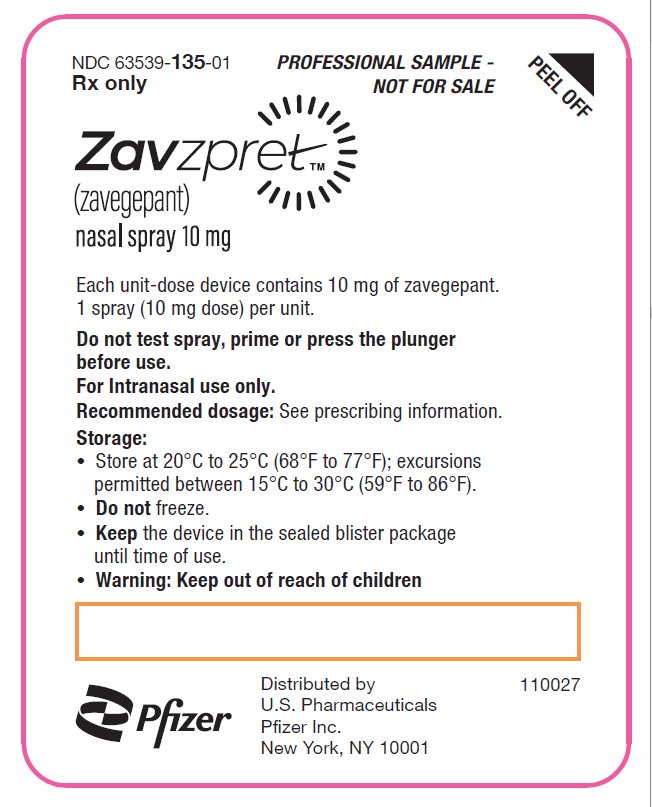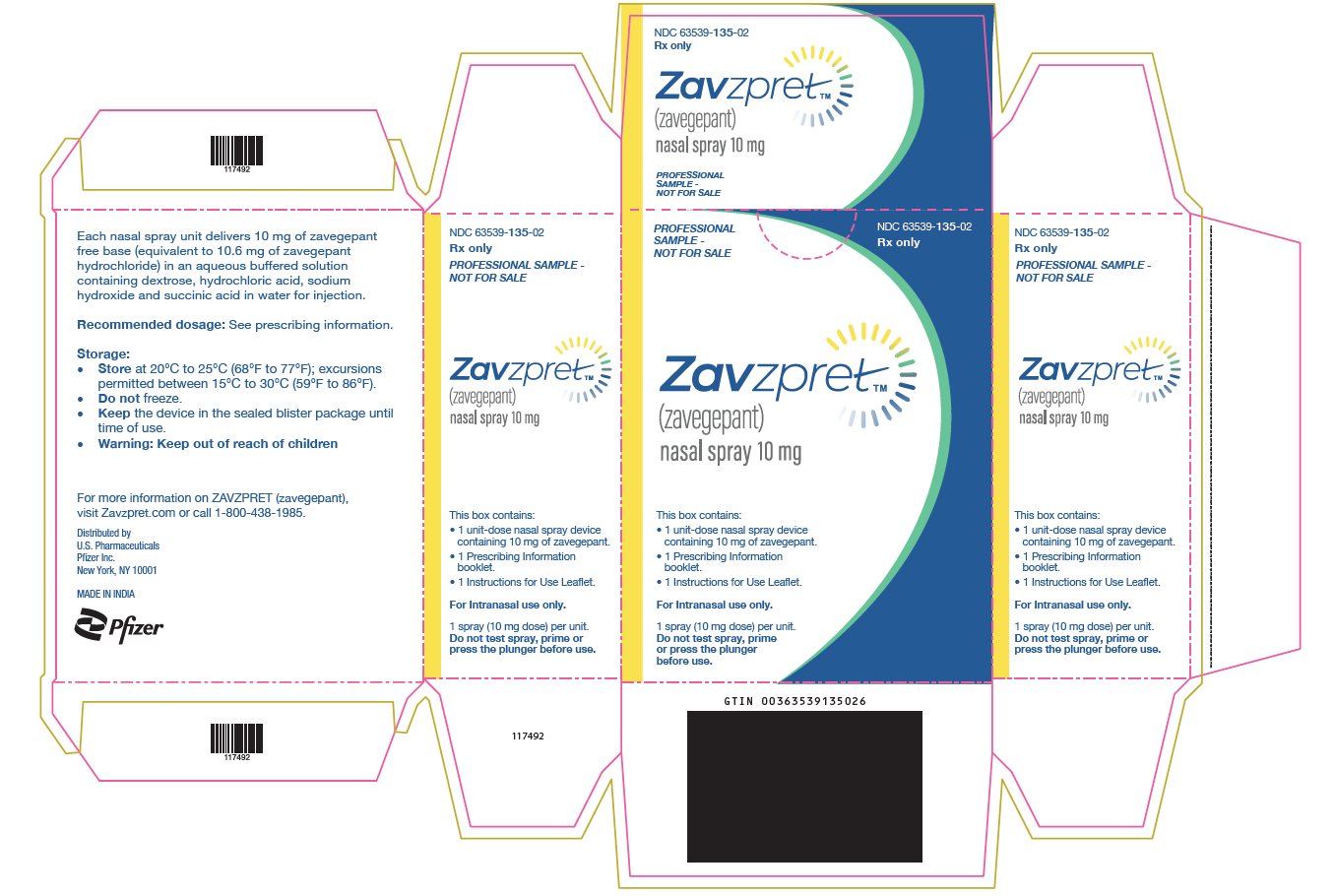 DRUG LABEL: ZAVZPRET
NDC: 63539-135 | Form: SPRAY
Manufacturer: U.S. Pharmaceuticals
Category: prescription | Type: HUMAN PRESCRIPTION DRUG LABEL
Date: 20251226

ACTIVE INGREDIENTS: ZAVEGEPANT HYDROCHLORIDE 10 mg/0.1 mL
INACTIVE INGREDIENTS: SUCCINIC ACID 0.59 mg/0.1 mL; ANHYDROUS DEXTROSE 1.25 mg/0.1 mL; HYDROCHLORIC ACID; SODIUM HYDROXIDE; WATER

HIGHLIGHTS OF PRESCRIBING INFORMATION

These highlights do not include all the information needed to use ZAVZPRET safely and effectively. See full prescribing information for ZAVZPRET.
ZAVZPRET™ (zavegepant) nasal spray
Initial U.S. Approval: 2023

RECENT MAJOR CHANGES

Contraindications (4) | 8/2025
Warnings and Precautions (5.1) | 8/2025
Warnings and Precautions (5.2, 5.3) | 3/2025

1 INDICATIONS AND USAGE

ZAVZPRET is a calcitonin gene-related peptide receptor antagonist indicated for the acute treatment of migraine with or without aura in adults. (1)

Limitations of Use

ZAVZPRET is not indicated for the preventive treatment of migraine. (1)

2 DOSAGE AND ADMINISTRATION

- The recommended dose is 10 mg given as a single spray in one nostril, as needed. (2.1)
- The maximum dose in a 24-hour period is 10 mg (one spray). (2.1)
- The safety of treating more than 8 migraines in a 30-day period has not been established. (2.1)

3 DOSAGE FORMS AND STRENGTHS

Nasal spray: 10 mg (3)

4 CONTRAINDICATIONS

Patients with a history of hypersensitivity reaction to zavegepant or to any of the components of ZAVZPRET. (4)

5 WARNINGS AND PRECAUTIONS

- Hypersensitivity Reactions: If a serious hypersensitivity reaction occurs, discontinue ZAVZPRET and initiate appropriate therapy. Hypersensitivity reactions including anaphylaxis, facial swelling, and urticaria, have occurred with ZAVZPRET. (5.1)
- Hypertension: New-onset or worsening of pre-existing hypertension may occur. (5.2)
- Raynaud’s Phenomenon: New-onset or worsening of pre-existing Raynaud’s phenomenon may occur. (5.3)

6 ADVERSE REACTIONS

Most common adverse reactions (at least 2% of patients treated with ZAVZPRET and greater than placebo) were taste disorders, nausea, nasal discomfort, and vomiting. (6.1)

To report SUSPECTED ADVERSE REACTIONS, contact Pfizer Inc. at 1-800-438-1985 or FDA at 1-800-FDA-1088 or www.fda.gov/medwatch.

7 DRUG INTERACTIONS

- Avoid use with drugs that inhibit OATP1B3 or NTCP transporters. (7.1)
- Avoid use with drugs that induce OATP1B3 or NTCP transporters. (7.2)
- Avoid use of intranasal decongestants; if unavoidable, administer intranasal decongestants at least 1 hour after ZAVZPRET administration. (7.3)

8 USE IN SPECIFIC POPULATIONS

- Avoid use in patients with severe hepatic impairment. (8.6)
- Avoid use in patients with CLcr < 30 mL/min. (8.7)

FULL PRESCRIBING INFORMATION

1 INDICATIONS AND USAGE

ZAVZPRET is indicated for the acute treatment of migraine with or without aura in adults.

Limitations of Use

ZAVZPRET is not indicated for the preventive treatment of migraine.

2 DOSAGE AND ADMINISTRATION

2.1 Dosing Information

The recommended dose of ZAVZPRET is 10 mg given as a single spray in one nostril, as needed.

The maximum dose that may be given in a 24-hour period is 10 mg (one spray). The safety of treating more than 8 migraines in a 30-day period has not been established.

3 DOSAGE FORMS AND STRENGTHS

Nasal spray: 10 mg of zavegepant per device. Each unit-dose nasal spray device delivers a single spray containing 10 mg of zavegepant.

4 CONTRAINDICATIONS

ZAVZPRET is contraindicated in patients with a history of hypersensitivity reaction to zavegepant or any of the components of ZAVZPRET. Reactions have included anaphylaxis [see Warnings and Precautions (5.1)].

5 WARNINGS AND PRECAUTIONS

5.1 Hypersensitivity Reactions

Serious hypersensitivity reactions, including anaphylaxis, facial swelling, and urticaria, have occurred in patients treated with ZAVZPRET. If a hypersensitivity reaction occurs, discontinue ZAVZPRET and initiate appropriate therapy [see Contraindications (4) and Adverse Reactions (6.1, 6.2)].

5.2 Hypertension

Development of hypertension and worsening of pre-existing hypertension have been reported following the use of CGRP antagonists in the postmarketing setting.

Some of the patients receiving a CGRP antagonist who developed new-onset hypertension had risk factors for hypertension. There were cases requiring initiation of pharmacological treatment for hypertension and, in some cases, hospitalization. Hypertension may occur at any time during treatment, but was most frequently reported within 7 days of therapy initiation. The CGRP antagonist was discontinued in many of the reported cases.

Monitor patients treated with ZAVZPRET for new-onset hypertension or worsening of pre-existing hypertension, and consider whether discontinuation of ZAVZPRET is warranted if evaluation fails to establish an alternative etiology or blood pressure is inadequately controlled.

5.3 Raynaud’s Phenomenon

Development of Raynaud’s phenomenon and recurrence or worsening of pre-existing Raynaud’s phenomenon have been reported in the postmarketing setting following the use of CGRP antagonists.

In reported cases with small molecule CGRP antagonists, symptom onset occurred a median of 1.5 days following dosing. Many of the cases reported serious outcomes, including hospitalizations and disability, generally related to debilitating pain. In most reported cases, discontinuation of the CGRP antagonist resulted in resolution of symptoms.

ZAVZPRET should be discontinued if signs or symptoms of Raynaud’s phenomenon develop, and patients should be evaluated by a healthcare provider if symptoms do not resolve. Patients with a history of Raynaud’s phenomenon should be monitored for, and informed about the possibility of, worsening or recurrence of signs and symptoms.

6 ADVERSE REACTIONS

The following clinically significant adverse reactions are discussed in greater detail in other sections of the labeling:

- Hypersensitivity Reactions [see Warnings and Precautions (5.1)]
- Hypertension [see Warnings and Precautions (5.2)]
- Raynaud’s Phenomenon [see Warnings and Precautions (5.3)]

6.1 Clinical Trials Experience

Because clinical trials are conducted under widely varying conditions, adverse reaction rates observed in the clinical trials of a drug cannot be directly compared to rates in the clinical trials of another drug and may not reflect the rates observed in clinical practice.

The safety of ZAVZPRET for the acute treatment of migraine in adults has been evaluated in two randomized, double-blind, placebo-controlled trials (Study 1 and Study 2) in patients with migraine who received one 10 mg dose of ZAVZPRET nasal spray (N=1023) or placebo (N=1056) [see Clinical Studies (14)]. Approximately 83% were female, 81% were White, 20% were Hispanic or Latino, and 15% were Black. The mean age at study entry was 41 years (range 18-79 years of age).

Adverse reactions in Study 1 and 2 are shown in Table 1.

Table 1: Adverse Reactions Occurring in At Least 2% of Patients Treated with ZAVZPRET and at a Frequency Greater than Placebo in Study 1 and 2

Adverse Reaction | ZAVZPRET; N=1023; % | Placebo; N=1056; %
Taste Disorders [Taste disorders includes dysgeusia and ageusia] | 18 | 4
Nausea | 4 | 1
Nasal Discomfort | 3 | 1
Vomiting | 2 | <1

Hypersensitivity, including facial swelling and urticaria, occurred in less than 1% of patients treated with ZAVZPRET [see Contraindications (4) and Warnings and Precautions (5.1)].

Long-term safety was assessed in an open-label extension study. That study evaluated 603 patients, dosing intermittently for up to one year, including 360 patients who were exposed to ZAVZPRET 10 mg for at least 6 months, and 298 who were exposed for at least one year, all of whom treated an average of at least two migraine attacks per month.

6.2 Postmarketing Experience

The following adverse reactions have been identified during postapproval use of ZAVZPRET. Because these reactions are reported voluntarily from a population of uncertain size, it is not always possible to reliably estimate their frequency or establish a causal relationship to drug exposure.

Immune System Disorders: Hypersensitivity (e.g., anaphylaxis) [see Contraindications (4) and Warnings and Precautions (5.1)]

Vascular Disorders: Hypertension [see Warnings and Precautions (5.2)], Raynaud’s phenomenon [see Warnings and Precautions (5.3)]

7 DRUG INTERACTIONS

7.1 OATP1B3 or NTCP Inhibitors

Concomitant administration of ZAVZPRET with inhibitors of the organic anion transporting polypeptide 1B3 (OATP1B3) or sodium taurocholate co-transporting polypeptide (NTCP) transporters may result in a significant increase in zavegepant exposure. Avoid concomitant administration of ZAVZPRET with drugs that inhibit OATP1B3 or NTCP transporters [see Clinical Pharmacology (12.3)].

7.2 OATP1B3 or NTCP Inducers

Concomitant administration of ZAVZPRET with inducers of OATP1B3 or NTCP transporters may result in a decrease in zavegepant exposure. Avoid concomitant administration of ZAVZPRET with drugs that induce OATP1B3 or NTCP transporters [see Clinical Pharmacology (12.3)].

7.3 Intranasal Decongestants

Concomitant administration of ZAVZPRET with intranasal decongestants may decrease the absorption of zavegepant. Avoid concomitant administration of intranasal decongestants with ZAVZPRET. When concomitant use is unavoidable, intranasal decongestants should be administered at least 1 hour after ZAVZPRET administration [see Clinical Pharmacology (12.3)].

8 USE IN SPECIFIC POPULATIONS

8.1 Pregnancy

Risk Summary

There are no adequate data on the developmental risk associated with the use of ZAVZPRET in pregnant women. No adverse developmental effects were observed following subcutaneous administration of zavegepant to pregnant animals at doses associated with plasma exposures higher than those used clinically (see Data).

In the U.S. general population, the estimated background risk of major birth defects and miscarriage in clinically recognized pregnancies is 2 to 4% and 15 to 20%, respectively. The estimated rate of major birth defects (2.2 to 2.9%) and miscarriage (17%) among deliveries to women with migraine are similar to rates reported in women without migraine.

Clinical Considerations

Disease-Associated Maternal and/or Embryo/Fetal Risk

Published data have suggested that women with migraine may be at increased risk of preeclampsia and gestational hypertension during pregnancy.

Data

Animal Data

Subcutaneous administration of zavegepant to pregnant rats (0, 10, 20, or 40 mg/kg/day) or rabbits (0, 20, 40, or 60 mg/kg/day) during the period of organogenesis resulted in no adverse effects on embryofetal development. Plasma exposures (AUC) at the highest doses tested were approximately 4000 times that in humans at the maximum recommended human dose (MRHD) of 10 mg/day.

Subcutaneous administration of zavegepant (0, 5, 10, or 20 mg/kg/day) to rats throughout pregnancy and lactation resulted in no adverse effects on pre- and postnatal development. Plasma exposure (AUC) at the highest dose tested was approximately 2500 times that in humans at the MRHD.

8.2 Lactation

There are no data on the presence of zavegepant or its metabolites in human milk, the effects of zavegepant on the breastfed infant, or the effects of zavegepant on milk production. The developmental and health benefits of breastfeeding should be considered along with the mother’s clinical need for ZAVZPRET and any potential adverse effects on the breastfed infant from ZAVZPRET or from the underlying maternal condition.

8.4 Pediatric Use

Safety and effectiveness in pediatric patients have not been established.

8.5 Geriatric Use

Clinical studies of ZAVZPRET did not include sufficient numbers of patients 65 years of age and older to determine whether they respond differently from younger adult patients.

In a limited number of patients 65 years of age and older, no clinically significant pharmacokinetic differences were observed between elderly and younger subjects.

8.6 Hepatic Impairment

No dosage adjustment of ZAVZPRET is necessary in patients with mild hepatic impairment (Child-Pugh Class A) or moderate hepatic impairment (Child-Pugh Class B). ZAVZPRET has not been studied in patients with severe hepatic impairment (Child-Pugh Class C). Avoid use of ZAVZPRET in patients with severe hepatic impairment [see Clinical Pharmacology (12.3)].

8.7 Renal Impairment

No dosage adjustment of ZAVZPRET is necessary in patients with estimated creatine clearance (CLcr) 30 mL/min or greater. Avoid use of ZAVZPRET in patients with CLcr less than 30 mL/min [see Clinical Pharmacology (12.3)].

11 DESCRIPTION

ZAVZPRET (zavegepant) nasal spray contains zavegepant hydrochloride, a calcitonin gene-related peptide receptor antagonist. Zavegepant hydrochloride is described chemically as (R)-N-(3-(7-methyl-1H-indazol-5-yl)-1-(4-(1-methylpiperidin-4-yl) piperazin-1-yl)-1-oxopropan-2-yl)-4-(2-oxo-1,2-dihydroquinolin-3-yl) piperidine-1-carboxamide hydrochloride and its structural formula is:

Its molecular formula is C36H46N8O3․HCl, representing a molecular weight of 675.28 g/mol. Zavegepant free base has a molecular weight of 638.82 g/mol. Zavegepant hydrochloride is a white to off-white powder, freely soluble in water, and has pKa values of 4.8 and 8.8.

Each unit-dose ZAVZPRET device for nasal administration delivers 10 mg of zavegepant (equivalent to 10.6 mg of zavegepant hydrochloride) in a buffered aqueous solution containing dextrose, hydrochloric acid, sodium hydroxide, and succinic acid in water for injection. The solution has a pH of 5.3 to 6.7.

12 CLINICAL PHARMACOLOGY

12.1 Mechanism of Action

Zavegepant is a calcitonin gene-related peptide (CGRP) receptor antagonist.

12.2 Pharmacodynamics

The relationship between pharmacodynamic activity and the mechanism by which zavegepant exerts its clinical effects is unknown.

No clinically relevant differences in resting blood pressure were observed when zavegepant was concomitantly administered with sumatriptan (12 mg subcutaneous, given as two 6 mg doses separated by one hour) compared with sumatriptan alone to healthy volunteers.

Cardiac Electrophysiology

At a dose up to 4 times the recommended daily dose, zavegepant does not prolong the QT interval to any clinically relevant extent.

12.3 Pharmacokinetics

Absorption

Peak plasma concentration of zavegepant was observed at approximately 30 minutes after a single 10 mg dose of the nasal spray. After nasal spray administration of zavegepant, the absolute bioavailability is approximately 5%.

Zavegepant given as a single dose of the nasal spray displays slightly less than dose-proportional pharmacokinetics up to 40 mg (approximately 4 times the recommended dosage of 10 mg).

Following once daily dosing of ZAVZPRET for 14 days there was no evidence of zavegepant accumulation.

Distribution

The mean apparent volume of distribution of intranasal zavegepant is approximately 1774 L. Plasma protein binding of zavegepant is approximately 90%.

Elimination

Metabolism

Zavegepant is primarily metabolized by CYP3A4 and to a lesser extent by CYP2D6, in vitro. After single IV dose of 5 mg [^14C]-zavegepant, unchanged zavegepant was the most prevalent (approximately 90%) circulating component in the human plasma. No major metabolites (i.e., greater than 10%) of zavegepant were detected in plasma.

Excretion

The effective half-life of zavegepant following a 10 mg dose of the nasal spray is 6.55 hours. The mean apparent clearance of intranasal zavegepant is 266 L/h. Zavegepant is excreted mostly via the biliary/fecal route, while the renal route is a minor route of elimination. Following a single intravenous dose of 5 mg [^14C]-zavegepant to healthy male subjects, approximately 80% and 11% of the dose was recovered as unchanged zavegepant in feces and urine, respectively.

Specific Populations

Patients with Hepatic Impairment

In a dedicated clinical study comparing the pharmacokinetics of zavegepant in subjects with moderate hepatic impairment (Child-Pugh B) to that of normal subjects (matched healthy controls), zavegepant Cmax was 16% higher and AUC was 1.9-fold higher in patients with moderate hepatic impairment. These changes in exposures are not expected to be clinically significant, based on clinical safety experience and minimal accumulation of drug exposures. The impact of severe hepatic impairment (Child-Pugh C) on the pharmacokinetics of zavegepant was not studied [see Use in Specific Populations (8.6)].

Patients with Renal Impairment

The renal route plays a minor role in the clearance of zavegepant. No clinically significant effect on the pharmacokinetics of zavegepant is expected in subjects with estimated creatinine clearance (CLcr) 30 mL/min or greater. In patients with CLcr 15 to 29 mL/min, accumulation of uremic solutes can cause an increase in zavegepant exposures by inhibiting OATP transporters. Zavegepant has not been studied in patients with CLcr less than 15 mL/min [see Use in Specific Populations (8.7)].

Other Specific Populations

Age, sex, race, ethnicity, and body weight did not show clinically significant effects on the pharmacokinetics of zavegepant.

Drug Interaction Studies

In Vitro Studies

Enzymes

Zavegepant is a substrate of CYP3A4 and to a lesser extent CYP2D6. Zavegepant is not an inducer of CYP1A2, 2B6, or 3A4, or an inhibitor of CYP1A2, CYP2C9, 2C19, 2B6, 2D6, 2C8, and 3A4 at clinically relevant concentrations.

Transporters

Zavegepant is a substrate for OATP1B3 and NTCP (see In Vivo studies).

Zavegepant is also a substrate for the transporters P-gp, MATE1, and MATE2-K. Considering the minor contribution of the renal pathway in the clearance of zavegepant, coadministration of zavegepant with inhibitors of P-gp, MATE1, and MATE2-K inhibitors is not expected to result in a clinically significant effect on zavegepant pharmacokinetics.

Zavegepant is not a substrate for BCRP, OATP1B1, OAT1, OAT3, OCT2, BSEP, MRP2, MRP3, and MRP4.

Zavegepant is an inhibitor of OCT2, MATE1, and MATE2-K, but drug interactions for ZAVZPRET are not expected at clinically relevant concentrations. Zavegepant is not an inhibitor of P-gp, BCRP, OAT1, OAT3, OATP1B1, and OATP1B3.

In Vivo Studies

CYP3A4 Inhibitors

Concomitant administration of a single dose of 10 mg ZAVZPRET with itraconazole (a strong CYP3A4 and P-gp inhibitor), at steady state did not result in a clinically relevant effect on the exposures of zavegepant.

OATP1B3 or NTCP Inhibitors

Concomitant administration of a single oral dose of 100 mg zavegepant with rifampin (an OATP1B3, NTCP inhibitor and a strong CYP3A inducer), at steady state resulted in increased zavegepant exposure (AUC by 2.3-fold and Cmax by 2.2-fold). The observed change in zavegepant exposures is a composite effect of inhibition of OATP1B3 and NTCP transporters as well as induction of CYP3A enzymes. Concomitant administration of ZAVZPRET with inhibitors of OATP1B3 or NTCP transporters may result in a significant increase in zavegepant exposure [see Drug Interactions (7.1)].

OATP1B3 or NTCP Inducers

Concomitant administration of ZAVZPRET with inducers of OATP1B3 or NTCP transporters has not been studied. However, since zavegepant is a substrate of OATP1B3 and NTCP, concomitant administration with inducers of these transporters may result in decreased zavegepant exposure [see Drug Interactions (7.2)].

Intranasal Decongestants

The effect of concomitant intranasal decongestants on the pharmacokinetics of zavegepant nasal spray has not been evaluated. Concomitant administration of intranasal decongestants may decrease the systemic exposure of zavegepant and potentially the efficacy of zavegepant [see Drug Interactions (7.3)].

Other Drugs

No significant pharmacokinetic interactions were observed when zavegepant was concomitantly administered with oral contraceptives (ethinyl estradiol) or sumatriptan [see Clinical Pharmacology (12.2)].

13 NONCLINICAL TOXICOLOGY

13.1 Carcinogenesis, Mutagenesis, Impairment of Fertility

Carcinogenesis

Intranasal administration of zavegepant (0, 0.3, 0.8, or 2.5 mg/day) to Tg.rasH2 mice for 26 weeks resulted in no evidence of drug-related tumors.

Intranasal administration of zavegepant (0, 2, 9, or 18.8 mg/kg/day) to rats for up to 96 weeks resulted in no evidence of drug-related tumors. Plasma exposure (AUC) at the highest dose tested was approximately 140 times that in humans at the maximum recommended human dose (MRHD) of 10 mg/day.

Mutagenesis

Zavegepant was negative in in vitro (bacterial reverse mutation, chromosomal aberration in Chinese hamster ovary cells) and in vivo (rat micronucleus) assays.

Impairment of Fertility

Subcutaneous administration of zavegepant (0, 5, 15, or 25 mg/kg/day) to male and female rats prior to and during mating and continuing in females to gestation day 7 resulted in no adverse effects on fertility or reproductive performance. Plasma exposures (AUC) at the highest dose tested were approximately 2800 times that in humans at MRHD.

14 CLINICAL STUDIES

The efficacy of ZAVZPRET for the acute treatment of migraine with or without aura in adults was demonstrated in two randomized, double-blind, placebo-controlled trials (Study 1 and Study 2). In both studies, patients were instructed to treat a migraine of moderate to severe headache pain intensity. Rescue medication (i.e., NSAIDs, acetaminophen, and/or an antiemetic) was allowed 2 hours after the initial treatment. Other forms of rescue medication such as triptans were not allowed within 48 hours of initial treatment. In Study 1 and Study 2, 13.4% and 13.6% of patients were taking preventive medications for migraine at baseline, respectively. None of the patients were on concomitant preventive medication that act on the CGRP pathway.

In Study 1 (NCT04571060), patients were randomized to receive a single dose of ZAVZPRET 10 mg (N=623) or placebo (N=646). Efficacy was demonstrated with ZAVZPRET 10 mg by an effect on the coprimary endpoints of pain freedom and most bothersome symptom (MBS) freedom at 2 hours after a single dose, compared to placebo. Pain freedom was defined as a reduction of moderate or severe headache pain to no headache pain, and MBS freedom was defined as the absence of the self-identified MBS (i.e., photophobia, phonophobia, or nausea). The most common MBS reported before dosing was photophobia (55%), followed by nausea (28%), and phonophobia (16%).

In Study 1, the percentage of patients achieving headache pain freedom and MBS freedom 2 hours after a single dose was statistically significantly greater in patients who received ZAVZPRET compared to those who received placebo (Table 2).

Table 2: Efficacy Endpoints in Study 1

 | ZAVZPRET; 10 mg | Placebo
Pain Free at 2 hours
n/N [n=number of responders/N=number of patients in that treatment group] | 147/623 | 96/646
% Responders | 23.6 | 14.9
Difference from placebo (%) | 8.8
p-value | <0.001
MBS [MBS = most bothersome symptoms of photophobia, phonophobia, or nausea.] Free at 2 hours
n/N | 247/623 | 201/646
% Responders | 39.6 | 31.1
Difference from placebo (%) | 8.7
p-value | 0.001

Figures 1 and 2 present the percentage of patients achieving migraine pain freedom and MBS freedom within 2 hours following treatment in Study 1.

Figure 1: Percentage of Patients Achieving Pain Freedom within 2 Hours in Study 1

Figure 2: Percentage of Patients Achieving MBS Freedom within 2 Hours in Study 1

In Study 1, statistically significant effects of ZAVZPRET compared to placebo were demonstrated for the additional efficacy endpoints of pain relief at 2 hours post-dose, return to normal function at 2 hours post-dose, sustained pain freedom from 2 to 48 hours post-dose (Table 3), and phonophobia and photophobia freedom at 2 hours post-dose. Pain relief was defined as a reduction in migraine pain from moderate or severe severity to mild or none. The measurement of the percentage of patients reporting normal function at two hours after dosing was derived from a single item questionnaire, asking patients to select one response on a 4-point scale: normal function, mild impairment, severe impairment, or required bedrest.

Table 3: Additional Efficacy Endpoints in Study 1

 | ZAVZPRET; 10 mg | Placebo
Pain Relief at 2 hours
n/N [n=number of responders/N=number of patients in that treatment group] | 366/623 | 321/646
% Responders | 58.7 | 49.7
Difference from placebo (%) | 9.0
p-value | 0.001
Percentage of Patients Reporting Normal Function at 2 hours [Includes patients with functional disability at time of dosing, according to the functional disability scale.]
n/N | 204/570 | 152/593
% Responders | 35.8 | 25.6
Difference from placebo (%) | 10.2
p-value | <0.001
Sustained Pain Freedom from 2 to 48 hours
n/N | 77/623 | 56/646
% Responders | 12.4 | 8.7
Difference from placebo (%) | 3.7
p-value | 0.031

The incidence of photophobia and phonophobia was reduced following administration of ZAVZPRET 10 mg as compared to placebo.

In Study 2 (NCT03872453), patients were randomized to receive a single dose of ZAVZPRET 10 mg (n=391) or placebo (n=401).

In Study 2, statistically significant efficacy was demonstrated with ZAVZPRET 10 mg by an effect on the coprimary endpoints of pain freedom and most bothersome symptom (MBS) freedom at 2 hours after a single dose, compared to placebo. Pain freedom was observed in 22.5% of patients receiving ZAVZPRET and 15.5% of patients receiving placebo (p-value = 0.011). MBS freedom was observed in 41.9% of patients receiving ZAVZPRET and 33.7% of patients receiving placebo (p-value = 0.016). The most common MBS reported before dosing was photophobia (53%), followed by nausea (31%), and phonophobia (15%).

Table 4: Efficacy Endpoints in Study 2

 | ZAVZPRET; 10 mg | Placebo
Pain Free at 2 hours
n/N [n=number of responders/N=number of patients in that treatment group] | 88/391 | 62/401
% Responders | 22.5 | 15.5
Difference from placebo (%) | 7.0
p-value | 0.011
MBS [MBS = most bothersome symptoms of photophobia, phonophobia, or nausea.] Free at 2 hours
n/N | 164/391 | 135/401
% Responders | 41.9 | 33.7
Difference from placebo (%) | 8.3
p-value | 0.016

Figure 3: Percentage of Patients Achieving Pain Freedom within 2 Hours in Study 2

Figure 4: Percentage of Patients Achieving MBS Freedom within 2 Hours in Study 2

16 HOW SUPPLIED/STORAGE AND HANDLING

16.1 How Supplied

ZAVZPRET nasal spray (NDC 0069-3500-01) contains 10 mg zavegepant and is supplied as a ready-to-use, unit-dose disposable device.

Each carton contains 6 units (NDC 0069-3500-02) and a Patient Information and Instructions for Use leaflet.

16.2 Storage and Handling

Store ZAVZPRET at controlled room temperature, 20°C to 25°C (68°F to 77°F); with excursions permitted between 15°C to 30°C (59°F to 86°F) [see USP controlled room temperature].

Do not freeze. Do not test spray, prime, or press the plunger before use.

17 PATIENT COUNSELING INFORMATION

Advise patients to read the FDA-approved patient labeling (Patient Information and Instructions for Use).

Hypersensitivity Reactions

Inform patients about the signs and symptoms of hypersensitivity reactions, and that these reactions can occur after administration of ZAVZPRET. Advise patients to contact their healthcare provider immediately if signs or symptoms of hypersensitivity reactions occur [see Warnings and Precautions (5.1)].

Hypertension

Inform patients that hypertension can develop or pre-existing hypertension can worsen with ZAVZPRET, and that they should contact their healthcare provider if they experience elevation in their blood pressure [see Warnings and Precautions (5.2)].

Raynaud’s Phenomenon

Inform patients that Raynaud’s phenomenon can develop or worsen with ZAVZPRET. Advise patients to discontinue ZAVZPRET and contact their healthcare provider if they experience signs or symptoms of Raynaud’s phenomenon [see Warnings and Precautions (5.3)].

Drug Interactions

Advise patients to speak with their healthcare provider about any prescription or over-the-counter medications or herbal supplements that they take or plan to take. Inform patients that if they need to use an intranasal decongestant it should be administered at least 1 hour after ZAVZPRET administration [see Drug Interactions (7.3)].

This product’s labeling may have been updated. For the most recent prescribing information, please visit www.pfizer.com.

LAB-1544-3.0

Patient Package Insert

PATIENT INFORMATION
ZAVZPRET™ (zav-spret)

(zavegepant)

nasal spray

What is ZAVZPRET?

ZAVZPRET is a prescription medicine used in adults for the acute treatment of migraine attacks with or without aura.

ZAVZPRET is not used to prevent migraine attacks.

It is not known if ZAVZPRET is safe and effective in children.

Do not use ZAVZPRET if you are:

- allergic to zavegepant, or any of the ingredients in ZAVZPRET.

See the end of this leaflet for a complete list of ingredients in ZAVZPRET.

Before you use ZAVZPRET, tell your healthcare provider about all of your medical conditions, including if you:

- have high blood pressure.
- have circulation problems in your fingers and toes.
- have kidney problems.
- have liver problems.
- are pregnant or plan to become pregnant. It is not known if ZAVZPRET will harm your unborn baby.
- are breastfeeding or plan to breastfeed. It is not known whether ZAVZPRET passes into your breast milk. Talk with your healthcare provider about the best way to feed your baby if you use ZAVZPRET.

Tell your healthcare provider about all the medicines you take, including prescription and over-the-counter medicines, vitamins, and herbal supplements.

How should I use ZAVZPRET?

- Use ZAVZPRET exactly how your healthcare provider tells you to use it.
- See the Instructions for Use for complete information on how to use ZAVZPRET nasal spray.
- ZAVZPRET is given in the nose (nasal) only.
- Each ZAVZPRET only sprays 1 time and cannot be reused. Do not test or prime the nasal spray before use.
- Each dose of ZAVZPRET is provided in an individual pack. Use all of the medicine in 1 pack for a complete dose.
- The recommended dose is 10 mg given as a single spray in one nostril.
- Do not use more than 1 spray (10 mg) of ZAVZPRET nasal spray in a 24-hour period.
- It is not known if it is safe to use more than 8 sprays (doses) of ZAVZPRET in 30 days.
- Avoid using intranasal decongestants with ZAVZPRET. If you have to use an intranasal decongestant, use it at least 1 hour after using ZAVZPRET.

What are the possible side effects of ZAVZPRET?

ZAVZPRET may cause serious side effects including:

- Allergic reactions. Allergic reactions, including trouble breathing, hives, and swelling of the face, can happen after you use ZAVZPRET. Call your healthcare provider or get emergency help right away if you have any of the following symptoms, which may be part of an allergic reaction:
  - swelling of the face, mouth, tongue, or throat
  - trouble breathing
  - rash
  - hives
- High blood pressure. High blood pressure or worsening of high blood pressure can happen after you use ZAVZPRET. Contact your healthcare provider if you have an increase in blood pressure.
- Raynaud’s phenomenon. A type of circulation problem can worsen or happen after you use ZAVZPRET. Raynaud’s phenomenon can lead to your fingers or toes feeling numb, cool, or painful, or changing color from pale, to blue, to red. Contact your healthcare provider if these symptoms occur.

The most common side effects of ZAVZPRET are:

- unusual taste
- nausea
- nasal discomfort
- vomiting

These are not the only possible side effects of ZAVZPRET.

Call your doctor for medical advice about side effects. You may report side effects to FDA at 1-800-FDA-1088.

How should I store ZAVZPRET?

- Store ZAVZPRET in the blister package that it comes in.
- Store ZAVZPRET at room temperature between 68°F to 77°F (20°C to 25°C).
- Do not freeze.

Keep ZAVZPRET and all medicines out of the reach of children.

General information about the safe and effective use of ZAVZPRET:

Medicines are sometimes prescribed for purposes other than those listed in a Patient Information leaflet. Do not use ZAVZPRET for a condition for which it was not prescribed. Do not give ZAVZPRET to other people, even if they have the same symptoms that you have. It may harm them. You can ask your pharmacist or healthcare provider for information about ZAVZPRET that is written for health professionals.

What are the ingredients in ZAVZPRET?

Active ingredients in ZAVZPRET: zavegepant

Inactive ingredients in ZAVZPRET: dextrose, hydrochloric acid, sodium hydroxide, and succinic acid in water for injection.

For more information, go to www.zavzpret.com or call 1-800-438-1985.

LAB-1545-3.0

This Patient Information has been approved by the US. Food and Drug Administration | 8/2025

Instructions for Use

ZAVZPRET [zav-spret]
(zavegepant) nasal spray
For Nasal Use Only
This Instructions for Use contains information on how to give a single dose (10 mg) with ZAVZPRET nasal spray
One (1) device delivers a single dose of ZAVZPRET. The device provides 1 spray that should be delivered into 1 nostril.
ZAVZPRET Device Parts
Important Information You Need to Know Before Dosing with ZAVZPRET
- For nasal use only (spray into nose).
- Do not spray in the eyes.
- Keep ZAVZPRET and all medicines out of reach of children.
- Do not use if the expiration (EXP) date has passed. Throw away the expired device in the trash if the expiration (EXP) date has passed.
- Do not remove the device from its blister packaging until you are ready to use it.
- Do not test spray, prime, or press the plunger before dosing. Each device is single use and can only be used 1 time. If you press the plunger before dosing, the spray will be lost, and the device will no longer function.
- Do not try to spray (dose) into more than 1 nostril. A dose is 1 spray into 1 nostril.
- Do not use more than 1 dose in a 24-hour period. Only 1 dose can be used per day.
- Do not use more than 8 doses per month. A maximum of 8 doses can be used per month.
Storage Information
- The device should be stored at room temperature between 68°F to 77°F (20°C to 25°C).
- Do not freeze.
- Keep the device in the sealed blister package until time of use.
- Keep ZAVZPRET and all medicines out of reach of children.
Preparing to Dose with ZAVZPRET Nasal Spray
1 | Gently Blow Your Nose
1.1 | Before using ZAVZPRET, blow your nose to clear your nostrils (see Figure B). This can be done while sitting or standing.
2 | Remove 1 Blister from the Carton
2.1 | Remove 1 blister containing a device from the carton (see Figure C).
3 | Check Expiration Date on the Blister
3.1 | Check the expiration date on the blister containing a device (see Figure D).
 | Do not use if the expiration date has passed. Throw away the expired device in the trash if the expiration date has passed.
4 | Remove Device from Blister
4.1 | Peel open the blister seal from the corner and remove it completely (see Figure E).
4.2 | Carefully remove the device from the plastic tray.
Dosing with ZAVZPRET Nasal Spray
5 | Check Expiration Date on the Device
5.1 | Check the expiration date on the device (see Figure F).; Do not use if the expiration date has passed. Throw away the expired device in the trash if the expiration date has passed.
6 | Grip the Device
6.1 | Hold the device upright with your thumb on the bottom of the plunger and two fingers on either side of the nozzle (see Figure G).; Do not press the plunger yet. If you press the plunger now, the medicine will spray and be wasted.
Dosing with ZAVZPRET Nasal Spray (Continued)
7 | Close 1 Nostril
7.1 | With your free hand, gently press 1 nostril to close it (see Figure H).
7.2 | Continue breathing normally through your mouth.
8 | Insert Spray Nozzle Into Open Nostril
8.1 | Insert the nozzle into the open nostril as much as you comfortably can (see Figure I).
9 |  | Deliver the Dose by Spraying Into Nostril and Breathing In
9.1 |  | Keep your head level and upright and close your mouth.; Do not tilt your head.; Do not lay down while delivering the dose.
9.2 |  | Slowly breathe in through your nose as you firmly press the plunger up with your thumb to release the spray (see Figure J).; Important: Hold the nozzle firmly in your nose as you deliver the dose. Do not let the nozzle come out when pressing the plunger.; Spray only 1 time into 1 nostril.
10 |  | Remove the Device and Keep Your Head Level for 20 Seconds
10.1 |  | Remove the device from your nostril and your finger from your other nostril.
10.2 |  | While keeping your head level and upright, gently breathe in through your nose and out through your mouth for 10 to 20 seconds (see Figure K).
If you feel a drip from your nose, gently sniff so you do not lose any of your dose.
Throwing away (Disposing of) Device
11 |  | Throw Away Used Device
11.1 |  | Throw away the used device into trash (see Figure L)
You have received your full dose, if you have:
✓ Used 1 device
✓ Given 1 spray into 1 nostril
Additional Information
For more information on ZAVZPRET (zavegepant), visit www.zavzpret.com or call 1-800-438-1985.
This Instructions for Use has been approved by the U.S. Food and Drug Administration Approved: 7/2024
LAB-1546-2.0

PRINCIPAL DISPLAY PANEL – Nasal Spray Device Label Front Sample

ZavzpretTM
(zavegepant)
nasal spray
10 mg

PROFESSIONAL SAMPLE –NOT FOR SALE
For intranasal use only
NDC 63539-135-01
Rx only

Do not test spray,
prime or press the
plunger before use.

PRINCIPAL DISPLAY PANEL – Nasal Spray Device Label Back Sample

U.S. Pharmaceuticals
Pfizer Inc.

LOT xxxxxxx
EXP YYYY-MM

PRINCIPAL DISPLAY PANEL – Nasal Spray Blister Foil Label Sample

NDC 63539-135-01
Rx only

PROFESSIONAL SAMPLE –
NOT FOR SALE

PEEL OFF

ZavzpretTM
(zavegepant)
nasal spray 10 mg

Each unit-dose device contains 10 mg of zavegepant.
1 spray (10 mg dose) per unit.
Do not test spray, prime or press the plunger
before use.
For Intranasal use only.
Recommended dosage: See prescribing information.
Storage:
• Store at 20°C to 25°C (68°F to 77°F); excursions
permitted between 15°C to 30°C (59°F to 86°F).
• Do not freeze.
• Keep the device in the sealed blister package
until time of use.
• Warning: Keep out of reach of children

Pfizer
Distributed by
U.S. Pharmaceuticals
Pfizer Inc.
New York, NY 10001

PRINCIPAL DISPLAY PANEL – Nasal Spray Carton Sample

PROFESSIONAL
SAMPLE -
NOT FOR SALE

NDC 63539-135-02
Rx only

ZavzpretTM
(zavegepant)
nasal spray 10 mg

This box contains:
• 1 unit-dose nasal spray device
containing 10 mg of zavegepant.
• 1 Prescribing Information
booklet.
• 1 Instructions for Use Leaflet.

For Intranasal use only.

1 spray (10 mg dose) per unit.
Do not test spray, prime
or press the plunger
before use.